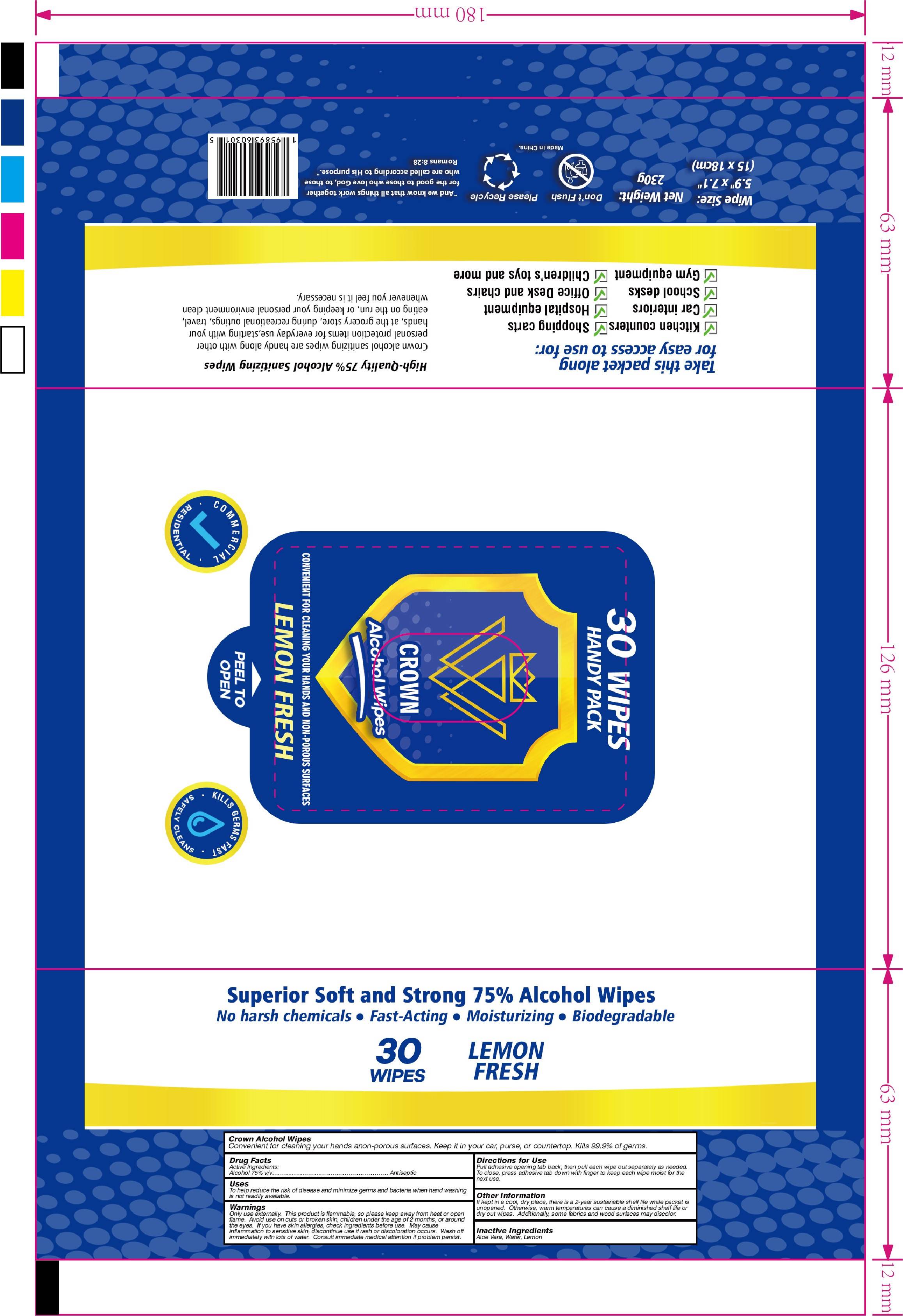 DRUG LABEL: Alcohol Wipes
NDC: 82534-101 | Form: CLOTH
Manufacturer: Hangzhou Beite Daily Necessities Co., Ltd.
Category: otc | Type: HUMAN OTC DRUG LABEL
Date: 20220127

ACTIVE INGREDIENTS: ALCOHOL 3.5 mL/1 1
INACTIVE INGREDIENTS: WATER; LIMONENE, (+)-; ALOE VERA LEAF

75% Alcohol Wipes

Active Ingredient(s)

Alcohol, 75% v/v. Purpose: Antiseptic

Purpose

Antiseptic

Uses

To help reduce the risk of disease and minimize germs and bacteria when hand washing is not readily available.

Warnings

Only use externally. This product is flammable, so please keep away from heat or open flame.

Avoid use on cuts or broken skin, children under the age of 2 months, or around the eyes.

If you have skin allergies, check ingredients before use.

May cause inflammation to sensitive skin, discontinue use if rash or discoloration occurs. Wash off immediately with lots of water. Cosult immediate medical attention if problem persist.

DO NOT USE

Avoid use on cuts or broken skin, children under the age of 2 months, or around the eyes.

If you have skin allergies, check ingredients before use.

WHEN USING

Avoid use on cuts or broken skin, children under the age of 2 months, or around the eyes.

If you have skin allergies, check ingredients before use.

STOP USE

May cause inflammation to sensitive skin, discontinue use if rash or discoloration occurs. Wash off immediately with lots of water. Cosult immediate medical attention if problem persist.

Keep out of reach of children.

Directions for Use

Pull adhesive opening tab back, then pull each wipe out seareately as needed.

To close, press adhesive tab down with finger to keep each wipe moist for the next use.

Other information

If kept in a cool, dry place, there is a 2-year sustainable shelf life while packet is unopen.

Otherwise, warm temperatures can cause a diminished shelf life or dry out wipes.

Additionally, some fabrics and wood surfaces may discolor.

Inactive Ingredient(s)

Aloe Vera, Water, Lemon